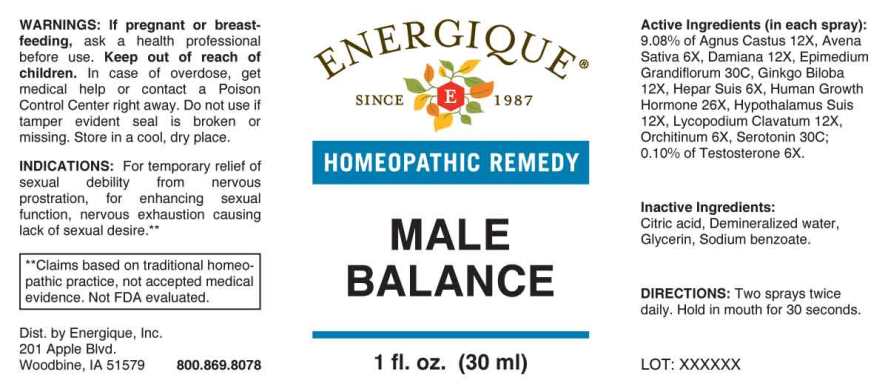 DRUG LABEL: Male Balance
NDC: 44911-0613 | Form: LIQUID
Manufacturer: Energique,Inc.
Category: homeopathic | Type: HUMAN OTC DRUG LABEL
Date: 20240426
DEA Schedule: CIII

ACTIVE INGREDIENTS: AVENA SATIVA FLOWERING TOP 6 [hp_X]/1 mL; PORK LIVER 6 [hp_X]/1 mL; SUS SCROFA TESTICLE 6 [hp_X]/1 mL; TESTOSTERONE 6 [hp_X]/1 mL; CHASTE TREE FRUIT 12 [hp_X]/1 mL; TURNERA DIFFUSA LEAFY TWIG 12 [hp_X]/1 mL; GINKGO 12 [hp_X]/1 mL; SUS SCROFA HYPOTHALAMUS 12 [hp_X]/1 mL; LYCOPODIUM CLAVATUM SPORE 12 [hp_X]/1 mL; SOMATROPIN 26 [hp_X]/1 mL; EPIMEDIUM GRANDIFLORUM TOP 30 [hp_X]/1 mL; SEROTONIN HYDROCHLORIDE 30 [hp_X]/1 mL
INACTIVE INGREDIENTS: ANHYDROUS CITRIC ACID; GLYCERIN; SODIUM BENZOATE; WATER

DRUG FACTS

ACTIVE INGREDIENTS

(in each spray): 6.66% of Agnus Castus 12X, Avena Sativa 6X, Damiana 12X, Epimedium Grandiflorum 30C, Ginkgo Biloba 12X, Hepar Suis 6X, Human Growth Hormone 26X, Hypothalamus (Suis) 12X, Lycopodium Clabatum 12X, Orchitinum (Suis) 6X, Serotonin (Hydrochloride) 30C, 0.10% of Testosterone 6X.

INDICATIONS:

For temporary relief of sexual debility from nervous prostration, for enhancing sexual function, nervous exhaustion causing lack of sexual desire.**

**Claims based on traditional homeopathic practice, not accepted medical evidence. Not FDA evaluated.

WARNINGS:

If pregnant or breast-feeding, ask a health professional before use.

Keep out of reach of children. In case of overdose, get medical help or contact a Poison Control Center right away.

Do not use if tamper evident seal is broken or missing.

Store in a cool, dry place.

Keep out of reach of children. In case of overdose, get medical help or contact a Poison Control Center right away.

DIRECTIONS:

Two sprays twice daily. Hold in mouth for 30 seconds.

INDICATIONS:

For temporary relief of sexual debility from nervous prostration, for enhancing sexual function, nervous exhaustion causing lack of sexual desire.**

**Claims based on traditional homeopathic practice, not accepted medical evidence. Not FDA evaluated.

INACTIVE INGREDIENTS:

Citric Acid, Demineralized Water, Glycerin, Sodium Benzoat

QUESTIONS:

Dist. by Energique, Inc.

201 Apple Blvd

Woodbine, IA 51579 800-869-8078

PACKAGE LABEL DISPLAY

ENERGIQUE

SINCE 1987

HOMEOPATHIC REMEDY

MALE BALANCE

1 fl. oz. (30 ml)